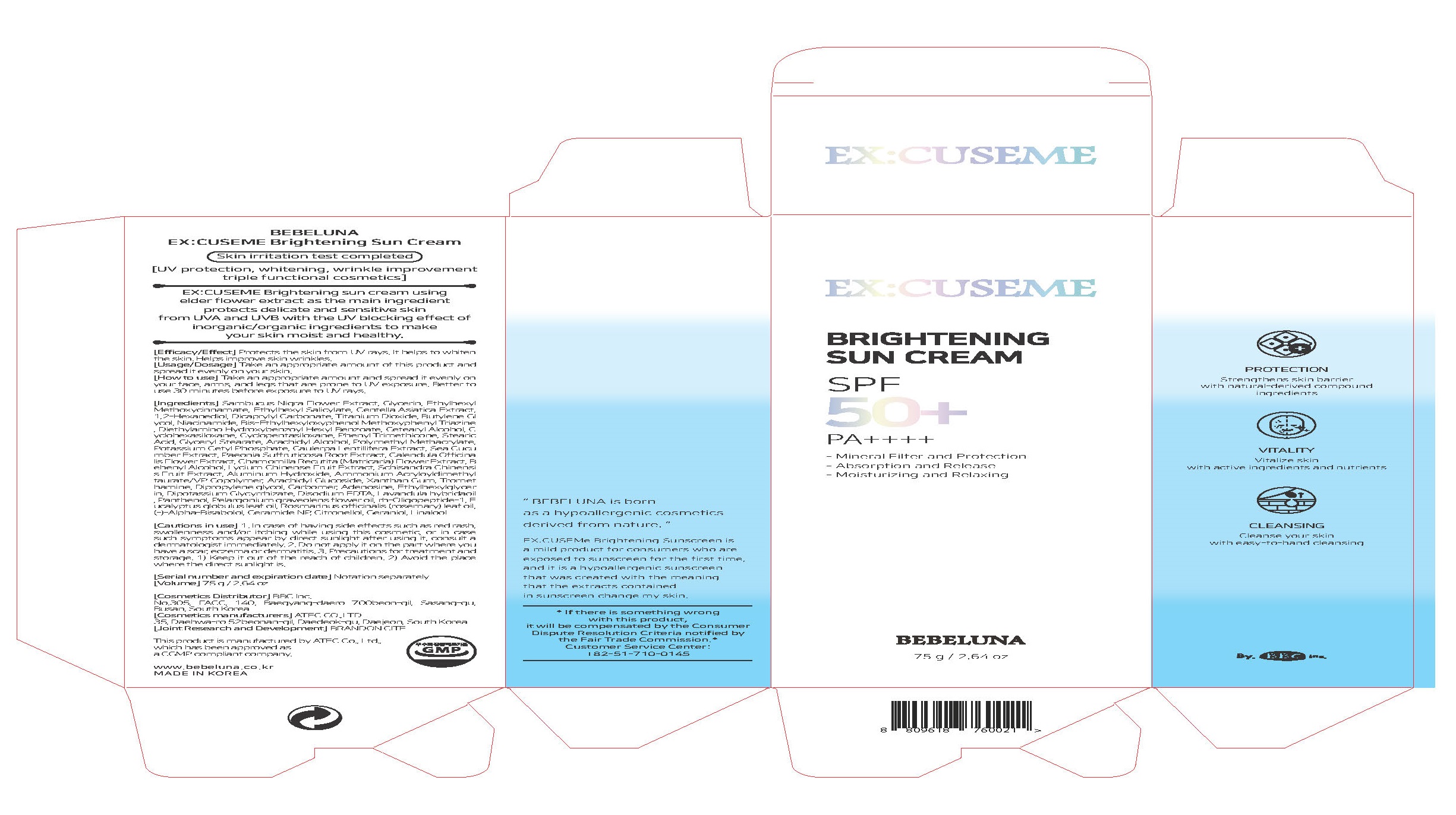 DRUG LABEL: EX CUSEME Brightening SunCream
NDC: 80785-0001 | Form: CREAM
Manufacturer: BBC Inc
Category: otc | Type: HUMAN OTC DRUG LABEL
Date: 20201017

ACTIVE INGREDIENTS: TITANIUM DIOXIDE 2.075 g/100 g
INACTIVE INGREDIENTS: ALUMINUM HYDROXIDE; WATER; GLYCERIN

ACTIVE INGREDIENT

titanium dioxide

PURPOSE

UV protection

skin whitening

wrinkle care

KEEP OUT OF REACH OF THE CHILDREN

WARNINGS

■ For external use only.

■ Do not use in eyes.

■ lf swallowed, get medical help promptly.

■ Stop use, ask doctor lf irritation occurs.

■ Keep out of reach of children.

DOSAGE AND ADMINISTRATION

for external use only

INACTIVE INGREDIENT

Sambucus Nigra Flower Extract
Glycerin
1,2-Hexanediol
Ethylhexylglycerin
Glycerin
Ethylhexyl Methoxycinnamate
Ethylhexyl Salicylate
Cyclopentasiloxane
Cyclohexasiloxane
Centella Asiatica Extract
1,2-Hexanediol
Dicaprylyl Carbonate
Aluminum Hydroxide
Stearic Acid
Niacinamide
Butylene Glycol
Bis-Ethylhexyloxyphenol Methoxyphenyl Triazine
Diethylamino Hydroxybenzoyl Hexyl Benzoate
Cetearyl Alcohol
1,2-Hexanediol
Arachidyl Alcohol
Behenyl Alcohol
Arachidyl Glucoside
Phenyl Trimethicone
Caulerpa Lentillifera Extract
Sea Cucumber Extract
1,2-Hexanediol
Paeonia Suffruticosa Root Extract
Schisandra Chinensis Fruit Extract
Lycium Chinense Fruit Extract
1,2-Hexanediol
Sambucus Nigra Flower Extract
Chamomilla Recutita (Matricaria) Flower Extract
Calendula Officinalis Flower Extract
1,2-Hexanediol
Glyceryl Stearate
Stearic Acid
Potassium Cetyl Phosphate
Polymethyl Methacrylate
Ammonium Acryloyldimethyltaurate/VP Copolymer
Xanthan Gum
Dipropylene glycol
Lavandula hybrida oil
Pelargonium graveolens flower oil
Rosmarinus officinalis (rosemary) leaf oil
Eucalyptus globulus leaf oil
Tromethamine
Carbomer
Adenosine
Dipotassium Glycyrrhizate
Disodium EDTA
Panthenol
rh-Oligopeptide-1
Ceramide NP
(-)-Alpha-Bisabolol

INDICATIONS AND USAGE

apply proper amount to the skin